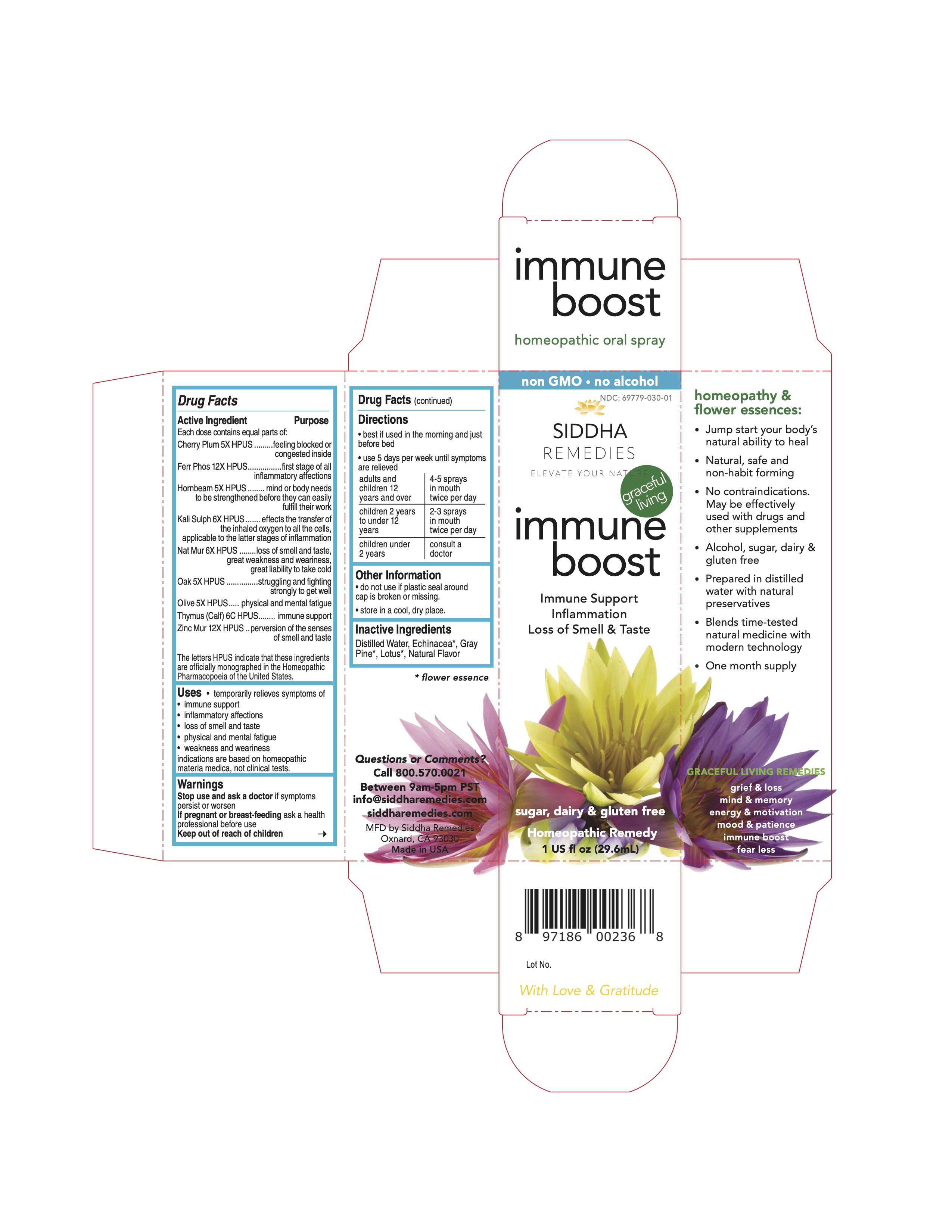 DRUG LABEL: Fear Less
NDC: 69779-029 | Form: SPRAY
Manufacturer: Siddha Flower Essences LLC
Category: homeopathic | Type: HUMAN OTC DRUG LABEL
Date: 20251231

ACTIVE INGREDIENTS: POPULUS TREMULA FLOWERING TOP 5 [hp_X]/29.6 mL; MAGNESIUM PHOSPHATE, TRIBASIC, PENTAHYDRATE 12 [hp_X]/29.6 mL; JUGLANS REGIA FLOWERING TOP 5 [hp_X]/29.6 mL; OYSTER SHELL CALCIUM CARBONATE, CRUDE 12 [hp_X]/29.6 mL; ULMUS PROCERA FLOWERING TWIG 5 [hp_X]/29.6 mL; POTASSIUM PHOSPHATE, UNSPECIFIED FORM 6 [hp_X]/29.6 mL; TRIBASIC CALCIUM PHOSPHATE 12 [hp_X]/29.6 mL; MIMULUS GUTTATUS FLOWERING TOP 5 [hp_X]/29.6 mL; ORNITHOGALUM UMBELLATUM FLOWERING TOP 5 [hp_X]/29.6 mL
INACTIVE INGREDIENTS: POTATO; WATER; MATRICARIA RECUTITA FLOWERING TOP

ACTIVE INGREDIENT

Each dose contains equal parts of:

Aspen 5X HPUS

Calc Carb 12X HPUS

Calc Phos 12X HPUS

Elm 5X HPUS

Kali Phos 6X HPUS

Mag Phos 12X HPUS

Mimulus 5X HPUS

Star of Bethlehem 5X HPUS

Walnut 5X HPUS

PURPOSE

Each dose contains equal parts of:

Aspen 5X HPUS ............vague unknown fears

Calc Carb 12X HPUS ........ full of fears, fear of being ill or unfortunate

Calc Phos 12X HPUS .......... depressed spirits, peevish and fretful

Elm 5X HPUS........... overwhelmed with things

Kali Phos 6X HPUS ....nervous dread; looks on the dark side of everything

Mag Phos 12X HPUS .... persistent depression of spirits

Mimulus 5X HPUS.....your anxieties cause you inner tension, well defined fears

Star of Bethlehem 5X HPUS..... after-effects of physical, mental, or emotional shock that occurred recently or long ago

Walnut 5X HPUS......constancy and protection from outside influences

The letters HPUS indicate that these ingredients are officially monographed in the Homeopathic Pharmacopoeia of the United States.

INDICATIONS AND USAGE

temporarily relieves symptoms of

• well defined fears
• vague unknown fears
• protection from outside influences

• nervous dread • overwhelmed

indications are based on homeopathic materia medica, not clinical tests.

Warnings
Stop use and ask a doctor if symptoms persist or worsen
If pregnant or breast-feeding ask a health professional before use
Keep out of reach of children

If pregnant or breast-feeding ask a

health professional before use

Keep out of reach of children

DOSAGE AND ADMINISTRATION

• best if used in the morning and just before bed

• use 5 days per week until symptoms are relieved

adults and children 12 years and over 4-5 sprays in mouth twice per day

children 2 years to under 12 years 2-3 sprays in mouth twice per day

children under 2 years consult a doctor

• do not use if plastic seal around cap is broken or missing.

• store in a cool, dry place.

INACTIVE INGREDIENT

Chamomile*, Distilled Water, Natural Flavor, Potato*

Questions or Comments?

Call 800.570.0021 Between 9am-5pm PST info@siddharemedies.com siddharemedies.com MFD by Siddha Remedies

Oxnard, CA 93030

Made in USA

Side Panel

homeopathy &

flower essences:

• Jump start your body’s

natural ability to heal

• Natural, safe and

non-habit forming

• No contraindications.

May be effectively

used with drugs and

other supplements

• Alcohol, sugar, dairy &

gluten free

• Prepared in distilled

water with natural

preservatives

• Blends time-tested

natural medicine with

modern technology

• One month supply

Full Warning Panel

Warnings

Stop use and ask a doctor if symptoms

persist or worsen

If pregnant or breast-feeding ask a

health professional before use

Keep out of reach of children

PACKAGE LABEL

non GMO • no alcohol

NDC: 69779-029-01

fear less

Well Defined Fears Vague Unknown Fears Fear of Being ill

sugar, dairy & gluten free

Homeopathic Remedy

1 US fl oz (29.6mL)